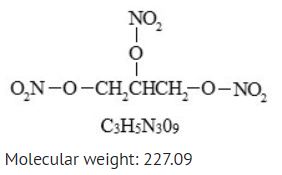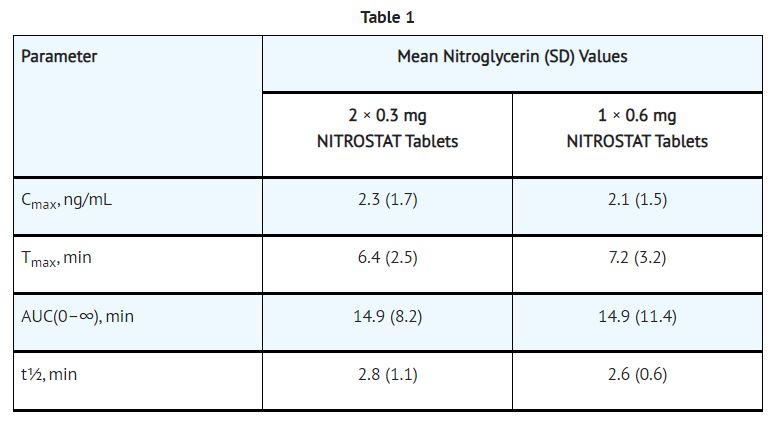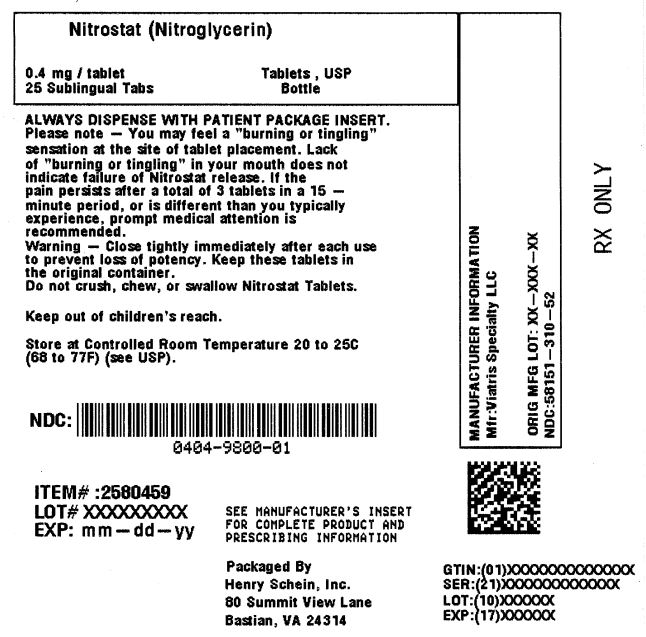 DRUG LABEL: NITROSTAT
NDC: 0404-9800 | Form: TABLET
Manufacturer: Henry Schein, Inc.
Category: prescription | Type: HUMAN PRESCRIPTION DRUG LABEL
Date: 20251106

ACTIVE INGREDIENTS: NITROGLYCERIN 0.4 mg/1 1
INACTIVE INGREDIENTS: LACTOSE MONOHYDRATE; GLYCERYL MONOSTEARATE; STARCH, CORN; CALCIUM SACCHARATE; SILICON DIOXIDE

HIGHLIGHTS OF PRESCRIBING INFORMATION

Nitrostat (Nitroglycerin Sublingual Tablets, USP)
These highlights do not include all the information needed to use NITROSTAT safely and effectively. See full prescribing information for NITROSTAT.
NITROSTAT (nitroglycerin) sublingual tablet
Initial U.S. Approval: 1981

1 INDICATIONS AND USAGE

INDICATIONS AND USAGE

NITROSTAT is a nitrate vasodilator indicated for relief of an attack or prophylaxis of angina pectoris due to coronary artery disease. (1)

2 DOSAGE AND ADMINISTRATION

DOSAGE AND ADMINISTRATION
• At the onset of an attack, administer one tablet under the tongue or buccal pouch. One additional tablet may be administered every 5 minutes as needed. No more than 3 total tablets are recommended within a 15 minute period. (2)
• If chest pain persists after three tablets, seek prompt medical attention. (2)
• May be used prophylactically 5 to 10 minutes prior to engaging in activities that might precipitate an acute attack. (2)

3 DOSAGE FORMS AND STRENGTHS

DOSAGE FORMS AND STRENGTHS
Sublingual tablets, 0.3 mg; 0.4 mg; 0.6 mg (3)

4 CONTRAINDICATIONS

CONTRAINDICATIONS
• Use of phosphodiesterase type 5 (PDE-5) inhibitors, such as avanafil, sildenafil, tadalafil, or vardenafil, or soluble guanylate cyclase (sGC) stimulators. (4.1, 7.1)
• Severe anemia (4.2)
• Increased intracranial pressure (4.3)
• Hypersensitivity to NITROSTAT or to other nitrates or nitrites or any excipient (4.4)
• Circulatory failure and shock (4.5)

5 WARNINGS AND PRECAUTIONS

WARNINGS AND PRECAUTIONS
• Tolerance: Excessive use may lead to tolerance. (5.1)
• Hypotension: Severe hypotension may occur. (5.2)

6 ADVERSE REACTIONS

ADVERSE REACTIONS
Most common adverse reactions occurring at a frequency greater than 2% are headache, dizziness and paresthesia. (6)

To report SUSPECTED ADVERSE REACTIONS, contact Viatris at 1-877-446-3679 (1-877-4-INFO-RX) or FDA at 1-800-FDA-1088 or www.fda.gov/medwatch.

7 DRUG INTERACTIONS

DRUG INTERACTIONS
Ergotamine: increased bioavailability of ergotamine. Avoid concomitant use. (7.2)

See 17 for PATIENT COUNSELING INFORMATION and FDA-approved patient labeling.

Revised: 2/2023

FULL PRESCRIBING INFORMATION

1 INDICATIONS AND USAGE

NITROSTAT is indicated for the acute relief of an attack or acute prophylaxis of angina pectoris due to coronary artery disease.

2 DOSAGE AND ADMINISTRATION

Administer one tablet under the tongue or in the buccal pouch at the first sign of an acute anginal attack. Allow tablet to dissolve without swallowing. One additional tablet may be administered every 5 minutes until relief is obtained. No more than three tablets are recommended within a 15-minute period. If the pain persists after a total of 3 tablets in a 15-minute period, or if the pain is different than is typically experienced, seek prompt medical attention.

NITROSTAT may be used prophylactically 5 to 10 minutes prior to engaging in activities that might precipitate an acute attack.

For patients with xerostomia, a small sip of water prior to placing the tablet under the tongue may help maintain mucosal hydration and aid dissolution of the tablet.

Administer NITROSTAT at rest, preferably in the sitting position.

3 DOSAGE FORMS AND STRENGTHS

NITROSTAT is supplied as white, round, flat-faced tablets in three strengths:

0.3 mg (Coded with “N” on one side and “3” on the other)
0.4 mg (Coded with “N” on one side and “4” on the other)
0.6 mg (Coded with “N” on one side and “6” on the other)

4 CONTRAINDICATIONS

4.1 PDE-5-Inhibitors and sGC-Stimulators
Do not use NITROSTAT in patients who are taking PDE-5 Inhibitors, such as avanafil, sildenafil, tadalafil, vardenafil hydrochloride. Concomitant use can cause severe hypotension, syncope, or myocardial ischemia [see Drug Interactions (7.1)].

Do not use NITROSTAT in patients who are taking the soluble guanylate cyclase stimulators, such as riociguat. Concomitant use can cause hypotension.

4.2 Severe Anemia
NITROSTAT is contraindicated in patients with severe anemia (large doses of nitroglycerin may cause oxidation of hemoglobin to methemoglobin and could exacerbate anemia).

4.3 Increased Intracranial Pressure
NITROSTAT may precipitate or aggravate increased intracranial pressure and thus should not be used in patients with possible increased intracranial pressure (e.g., cerebral hemorrhage or traumatic brain injury).

4.4 Hypersensitivity
NITROSTAT is contraindicated in patients who are allergic to nitroglycerin, other nitrates or nitrites or any excipient.

4.5 Circulatory Failure and Shock
NITROSTAT is contraindicated in patients with acute circulatory failure or shock.

5 WARNINGS AND PRECAUTIONS

5.1 Tolerance
Excessive use may lead to the development of tolerance. Only the smallest dose required for effective relief of the acute angina attack should be used. A decrease in therapeutic effect of sublingual nitroglycerin may result from use of long-acting nitrates.

5.2 Hypotension
Severe hypotension, particularly with upright posture, may occur with small doses of nitroglycerin particularly in patients with constrictive pericarditis, aortic or mitral stenosis, patients who may be volume-depleted, or are already hypotensive. Hypotension induced by nitroglycerin may be accompanied by paradoxical bradycardia and increased angina pectoris. Symptoms of severe hypotension (nausea, vomiting, weakness, pallor, perspiration and collapse/syncope) may occur even with therapeutic doses.

5.3 Hypertrophic Obstructive Cardiomyopathy
Nitrate therapy may aggravate the angina caused by hypertrophic cardiomyopathy.

5.4 Headache
Nitroglycerin produces dose-related headaches, especially at the start of nitroglycerin therapy, which may be severe and persist but usually subside with continued use.

6 ADVERSE REACTIONS

The following adverse reactions are discussed in more detail elsewhere in the label:

• Hypotension [see Warnings and Precautions (5.2)]
• Headache [see Warnings and Precautions (5.4)]
• Hypersensitivity [see Contraindications (4.4)]

Vertigo, dizziness, weakness, palpitation, and other manifestations of postural hypotension may develop occasionally, particularly in erect, immobile patients. Marked sensitivity to the hypotensive effects of nitrates (manifested by nausea, vomiting, weakness, diaphoresis, pallor, and collapse) may occur at therapeutic doses. Syncope due to nitrate vasodilatation has been reported.

Flushing, drug rash, and exfoliative dermatitis have been reported in patients receiving nitrate therapy.

7 DRUG INTERACTIONS

7.1 PDE-5-Inhibitors and sGC-Stimulators
NITROSTAT is contraindicated in patients who are using a selective inhibitor of cyclic guanosine monophosphate (cGMP)-specific phosphodiesterase type 5 (PDE-5). PDE-5-Inhibitors such as avanafil, sildenafil, vardenafil, and tadalafil have been shown to potentiate the hypotensive effects of organic nitrates.

NITROSTAT is contraindicated in patients who are taking soluble guanylate cyclase (sGC) stimulators. Concomitant use can cause hypotension.

The time course and dose dependence of these interactions have not been studied, and use within a few days of one another is not recommended. Appropriate supportive care for the severe hypotension has not been studied, but it seems reasonable to treat this as a nitrate overdose, with elevation of the extremities and with central volume expansion.

7.2 Ergotamine
Oral administration of nitroglycerin markedly decreases the first-pass metabolism of dihydroergotamine and subsequently increases its oral bioavailability. Ergotamine is known to precipitate angina pectoris. Therefore, patients receiving sublingual nitroglycerin should avoid ergotamine and related drugs or be monitored for symptoms of ergotism if this is not possible.

8 USE IN SPECIFIC POPULATIONS

8.1 Pregnancy

Risk SummaryLimited published data on the use of nitroglycerin are insufficient to determine a drug associated risk of major birth defects or miscarriage. In animal reproduction studies, there were no adverse developmental effects when nitroglycerin was administered intravenously to rabbits or intraperitoneally to rats during organogenesis at doses greater than 64-times the human dose [see Data].

The estimated background risk of major birth defects and miscarriage for the indicated population is unknown. In the U.S. general population, the estimated background risk of major birth defects and miscarriage in clinically recognized pregnancies is 2-4% and 15-20%, respectively.

Data

Animal Data
No embryotoxic or postnatal development effects were observed with transdermal application in pregnant rabbits and rats at doses up to 80 and 240 mg/kg/day, respectively, at intraperitoneal doses in pregnant rats up to 20 mg/kg/day from gestation day 7-17, and at intravenous doses in pregnant rabbits up to 4 mg/kg/day from gestation day 6-18.

8.2 Lactation

Risk Summary
Sublingual nitroglycerin has not been studied in lactating women. It is not known if nitroglycerin is present in human milk or if nitroglycerin has effects on milk production.

8.4 Pediatric Use
The safety and effectiveness of nitroglycerin in pediatric patients have not been established.

8.5 Geriatric Use
Clinical studies of NITROSTAT did not include sufficient numbers of subjects aged 65 and over to determine whether they respond differently from younger subjects. Other reported clinical experience has not identified differences in responses between the elderly and younger patients. In general, dose selection for an elderly patient should be cautious, usually starting at the low end of the dosing range, reflecting the greater frequency of decreased hepatic, renal, or cardiac function, and of concomitant disease or other drug therapy.

10 OVERDOSAGE

10.1 Signs and Symptoms, Methemoglobinemia
Nitrate overdosage may result in: severe hypotension, persistent throbbing headache, vertigo, palpitation, visual disturbance, flushing and perspiring skin (later becoming cold and cyanotic), nausea and vomiting (possibly with colic and even bloody diarrhea), syncope (especially in the upright posture), methemoglobinemia with cyanosis and anorexia, initial hyperpnea, dyspnea and slow breathing, slow pulse (dicrotic and intermittent), heart block, increased intracranial pressure with cerebral symptoms of confusion and moderate fever, paralysis and coma followed by clonic convulsions, and possibly death due to circulatory collapse.

Case reports of clinically significant methemoglobinemia are rare at conventional doses of organic nitrates. The formation of methemoglobin is dose-related and in the case of genetic abnormalities of hemoglobin that favor methemoglobin formation, even conventional doses of organic nitrates could produce harmful concentrations of methemoglobin.

10.2 Treatment of Overdosage
As hypotension associated with nitroglycerin overdose is the result of venodilatation and arterial hypovolemia, prudent therapy in this situation should be directed toward increase in central fluid volume. No specific antagonist to the vasodilator effects of nitroglycerin is known. Keep the patient recumbent in a shock position and comfortably warm. Passive movement of the extremities may aid venous return. Intravenous infusion of normal saline or similar fluid may also be necessary. Administer oxygen and artificial ventilation, if necessary. If methemoglobinemia is present, administration of methylene blue (1% solution), 1-2 mg per kilogram of body weight intravenously, may be required unless the patient is known to have G-6-PD deficiency. If an excessive quantity of nitroglycerin has been recently swallowed gastric lavage may be of use.

As epinephrine is ineffective in reversing the severe hypotensive events associated with overdosage, it is not recommended for resuscitation.

11 DESCRIPTION

NITROSTAT is a stabilized sublingual compressed nitroglycerin tablet that contains 0.3 mg, 0.4 mg , or 0.6 mg nitroglycerin; as well as lactose monohydrate, NF; glyceryl monostearate, NF; pregelatinized starch, NF; calcium stearate, NF powder; and silicon dioxide, colloidal, NF.

Nitroglycerin, an organic nitrate, is a vasodilating agent. The chemical name for nitroglycerin is 1, 2, 3 propanetriol trinitrate and the chemical structure is:

12 CLINICAL PHARMACOLOGY

12.1 Mechanism of Action
Nitroglycerin forms free radical nitric oxide (NO) which activates guanylate cyclase, resulting in an increase of guanosine 3'5' monophosphate (cyclic GMP) in smooth muscle and other tissues. These events lead to dephosphorylation of myosin light chains, which regulate the contractile state in smooth muscle, and result in vasodilatation.

12.2 Pharmacodynamics
The principal pharmacological action of nitroglycerin is relaxation of vascular smooth muscle. Although venous effects predominate, nitroglycerin produces, in a dose-related manner, dilation of both arterial and venous beds. Dilation of postcapillary vessels, including large veins, promotes peripheral pooling of blood, decreases venous return to the heart, and reduces left ventricular end-diastolic pressure (preload). Nitroglycerin also produces arteriolar relaxation, thereby reducing peripheral vascular resistance and arterial pressure (afterload), and dilates large epicardial coronary arteries; however, the extent to which this latter effect contributes to the relief of exertional angina is unclear.

Therapeutic doses of nitroglycerin may reduce systolic, diastolic, and mean arterial blood pressure. Effective coronary perfusion pressure is usually maintained, but can be compromised if blood pressure falls excessively, or increased heart rate decreases diastolic filling time.

Elevated central venous and pulmonary capillary wedge pressures, and pulmonary and systemic vascular resistance are also reduced by nitroglycerin therapy. Heart rate is usually slightly increased, presumably due to a compensatory response to the fall in blood pressure. Cardiac index may be increased, decreased, or unchanged. Myocardial oxygen consumption or demand (as measured by the pressure-rate product, tension-time index, and stroke-work index) is decreased and a more favorable supply-demand ratio can be achieved. Patients with elevated left ventricular filling pressures and increased systemic vascular resistance in association with a depressed cardiac index are likely to experience an improvement in cardiac index. In contrast, when filling pressures and cardiac index are normal, cardiac index may be slightly reduced following nitroglycerin administration.

Consistent with the symptomatic relief of angina, digital plethysmography indicates that onset of the vasodilatory effect occurs approximately 1 to 3 minutes after sublingual nitroglycerin administration and reaches a maximum by 5 minutes postdose. Effects persist for at least 25 minutes following NITROSTAT administration.

12.3 Pharmacokinetics
Absorption
Nitroglycerin is rapidly absorbed following sublingual administration of NITROSTAT tablets. Mean peak nitroglycerin plasma concentrations occur at a mean time of approximately 6 to 7 minutes postdose (Table 1). Maximum plasma nitroglycerin concentrations (Cmax) and area under the plasma concentration-time curves (AUC) increase dose-proportionally following 0.3 to 0.6 mg NITROSTAT. The absolute bioavailability of nitroglycerin from NITROSTAT tablets is approximately 40% but tends to be variable due to factors influencing drug absorption, such as sublingual hydration and mucosal metabolism.

Distribution
The volume of distribution (VArea) of nitroglycerin following intravenous administration is 3.3 L/kg. At plasma concentrations between 50 and 500 ng/mL, the binding of nitroglycerin to plasma proteins is approximately 60%, while that of 1,2- and 1,3-dinitroglycerin is 60% and 30%, respectively.

Metabolism
A liver reductase enzyme is of primary importance in the metabolism of nitroglycerin to glycerol di- and mononitrate metabolites and ultimately to glycerol and organic nitrate. Known sites of extrahepatic metabolism include red blood cells and vascular walls. In addition to nitroglycerin, 2 major metabolites 1,2- and 1,3‑dinitroglycerin, are found in plasma. Mean peak 1,2- and 1,3-dinitroglycerin plasma concentrations occur at approximately 15 minutes postdose. The elimination half-life of 1,2- and 1,3-dinitroglycerin is 36 and 32 minutes, respectively. The 1,2- and 1,3‑dinitroglycerin metabolites have been reported to possess approximately 2% and 10%, respectively, of the pharmacological activity of nitroglycerin. Higher plasma concentrations of the dinitro metabolites, along with their nearly 10-fold longer elimination half-lives, may contribute significantly to the duration of pharmacologic effect. Glycerol mononitrate metabolites of nitroglycerin are biologically inactive.

Elimination
Nitroglycerin plasma concentrations decrease rapidly, with a mean elimination half-life of 2 to 3 minutes. Half-life values range from 1.5 to 7.5 minutes. Clearance (13.6 L/min) greatly exceeds hepatic blood flow. Metabolism is the primary route of drug elimination.

Drug interactions
Aspirin
Coadministration of nitroglycerin with high dose aspirin (1000 mg) results in increased exposure to nitroglycerin. The vasodilatory and hemodynamic effects of nitroglycerin may be enhanced by concomitant administration of nitroglycerin with high dose aspirin.

Tissue-type plasminogen activator (t-PA)
Concomitant administration of t-PA and intravenous nitroglycerin has been shown to reduce plasma levels of t-PA and its thrombolytic effect.

13 NONCLINICAL TOXICOLOGY

13.1 Carcinogenesis, Mutagenesis, Impairment of Fertility
Animal carcinogenesis studies with sublingually administered nitroglycerin have not been performed.

Carcinogenicity potential of nitroglycerin was evaluated in rats receiving up to 434 mg/kg/day of dietary nitroglycerin for 2 years. Rats developed dose-related fibrotic and neoplastic changes in liver, including carcinomas, and interstitial cell tumors in testes. At high dose, the incidences of hepatocellular carcinomas in males was 48% and in females was 33%, compared to 0% in untreated controls. Incidences of testicular tumors were 52% vs. 8% in controls. Lifetime dietary administration of up to 1058 mg/kg/day of nitroglycerin was not tumorigenic in mice.

Nitroglycerin was mutagenic in Ames tests performed in 2 different laboratories. Nevertheless, there was no evidence of mutagenicity in an in vivo dominant lethal assay with male rats treated with doses up to about 363 mg/kg/day, PO, or in ex vivo cytogenetic tests in rat and dog cells.

In a 3-generation reproduction study, rats received dietary nitroglycerin at doses up to about 434 mg/kg/day for 6 months prior to mating of the F0 generation, with treatment continuing through successive F1 and F2 generations. The high dose was associated with decreased feed intake and body weight gain in both sexes at all matings. No specific effect on the fertility of the F0 generation was seen. Infertility noted in subsequent generations, however, was attributed to increased interstitial cell tissue and aspermatogenesis in the high-dose males. In this 3-generation study, there was no clear evidence of teratogenicity.

16 HOW SUPPLIED/STORAGE AND HANDLING

NITROSTAT is supplied as white, round, flat-faced tablets in 3 strengths (0.3 mg, 0.4 mg, and 0.6 mg) in bottles containing 100 tablets each, with color-coded labels, and in color-coded Patient Convenience Packages of 4 bottles of 25 tablets each.

0.3 mg: Coded N on one side and 3 on the other.
NDC 58151-309-01Bottle of 100 tablets

0.4 mg: Coded N on one side and 4 on the other.
NDC 58151-310-52Convenience Package
NDC 58151-310-01Bottle of 100 tablets

0.6 mg: Coded N on one side and 6 on the other.
NDC 58151-311-01Bottle of 100 tablets

Store at Controlled Room Temperature 20°25°C (68°77°F) [see USP]. Nitroglycerin should be kept in the original glass container and must be tightly capped after each use to prevent loss of tablet potency.

Product repackaged by: Henry Schein, Inc., Bastian, VA 24314
From Original Manufacturer/Distributor's NDC and Unit of Sale | To Henry Schein Repackaged Product NDC and Unit of Sale | Total Strength/Total Volume (Concentration) per unit
NDC 58151-310-52 Convenience Package 4 bottles of 25 tablets each | NDC 0404-9800-01 1 bottle in a bag (Bottle bears NDC 58151-310-94) | 0.4 mg

17 PATIENT COUNSELING INFORMATION

Advise the patient to read the FDA-approved patient labeling (Patient Information).

Distributed by:
Viatris Specialty LLC
Morgantown, WV 26505 U.S.A.

© 2023 Viatris Inc.

NITROSTAT is a registered trademark of Viatris Specialty LLC, a Viatris Company.

UPJ:NTRST:R1
Revised: 2/2023

Nitrostat® (Nitroglycerin Sublingual Tablets, USP)

Read this information carefully before you start NITROSTAT® (NYE-troe-stat) and each time you refill your prescription. There may be new information. This information does not replace talking with your doctor. If you have any questions about NITROSTAT, ask your doctor. Your doctor will know if NITROSTAT is right for you.

What is NITROSTAT?

NITROSTAT is a type of medicine known as an organic nitrate and is a vasodilating agent. It is used to treat a type of chest pain called angina.

What is Angina?

Angina is a pain or discomfort that keeps coming back when part of your heart does not get enough blood. Angina feels like a pressing or squeezing pain, usually in your chest under the breastbone. Sometimes you can feel it in your shoulders, arms, neck, jaws, or back. NITROSTAT can relieve this pain.

Who should not use NITROSTAT?

Do not use NITROSTAT if you are allergic to organic nitrates (like the active ingredient in NITROSTAT).

You should not take NITROSTAT if you have the following conditions:

• very recent heart attack
• severe anemia
• increased pressure in the head

Do not take NITROSTAT with drugs for erectile dysfunction, like VIAGRA® (sildenafil citrate), CIALIS® (tadalafil), or LEVITRA® (vardenafil hydrochloride), as this may lead to extreme lowering of your blood pressure.

Do not take NITROSTAT if you take medicines called guanylate cyclase stimulators which include riociguat, a medicine that treats pulmonary arterial hypertension and chronic‑thromboembolic pulmonary hypertension.

What should I tell my doctor before taking NITROSTAT?

Before using NITROSTAT, tell your doctor if:

• You are taking any medicines that are used to treat angina, heart failure, or an irregular heartbeat.
• You are taking any medicines that reduce blood pressure.
• You are taking any diuretics (water pills).
• You are taking medicines that can cause dry mouth such as tricyclic antidepressants (e.g. amitriptyline, desipramine, doxepin), anticholinergic drugs, or any antimuscarinic drugs (e.g. atropine).
• You are taking ergotamine or similar drugs for migraine headaches.
• You are taking aspirin.
• You are taking any medicines for erectile dysfunction.
• You are pregnant or plan to become pregnant.
• You are breastfeeding.

How should I take NITROSTAT?

• Do not chew, crush, or swallow NITROSTAT tablets.
• You should sit down when taking NITROSTAT tablets and use caution when you stand up. This eliminates the possibility of falling due to lightheadedness or dizziness.
• One tablet should be dissolved under the tongue or in the oral cavity at the first sign of chest pain.
• The dose may be repeated approximately every 5 minutes, until the chest pain is relieved.
• If the pain persists after a total of 3 tablets in a 15-minute period, or is different than you typically experience, call your doctor or seek emergency help.
• NITROSTAT may be used 5 to 10 minutes prior to activities that might cause chest pain.
• You may feel a burning or tingling sensation in your mouth when you take NITROSTAT.

What should I avoid while taking NITROSTAT?

• Do not breastfeed. It is not known if NITROSTAT will pass through your milk.
• Do not consume alcohol while taking NITROSTAT, as this can lower your blood pressure.
• Do not start any new prescription or non-prescription medicines or supplements, unless you check with your doctor first.

What are the possible side effects of NITROSTAT?

NITROSTAT may cause the following side effects:

• headache
• vertigo (a major symptom of balance disorder)
• dizziness
• weakness
• heart palpitations (unusual awareness of the heartbeat)
• low blood pressure upon rising from a seated position
• nausea and vomiting
• sweating
• paleness
• fainting
• flushing (warm or red condition of your skin)
• other skin reactions that may be severe

Tell your doctor if you are concerned about any side effects you experience. These are not all the possible side effects of NITROSTAT. For a complete list, ask your doctor or pharmacist.

How do I store NITROSTAT?

NITROSTAT should be kept in the original glass container and tightly capped after each use to prevent loss of tablet potency.

Store NITROSTAT tablets at room temperature (between 68° and 77°F).

General advice about NITROSTAT

Sometimes doctors will prescribe a medicine for a condition that is not included in the patient information leaflets. Only use NITROSTAT the way your doctor told you to. Do not give NITROSTAT to other people, even if they have the same symptoms you have. It may harm them.

You can ask your pharmacist or doctor for information about NITROSTAT, or contact Viatris at 1-877-446-3679 (1-877-4-INFO-RX).

Distributed by:
Viatris Specialty LLC
Morgantown, WV 26505 U.S.A.

© 2023 Viatris Inc.

NITROSTAT is a registered trademark of Viatris Specialty LLC, a Viatris Company.

UPJ:PL:NTRST:R1
Revised: 2/2023